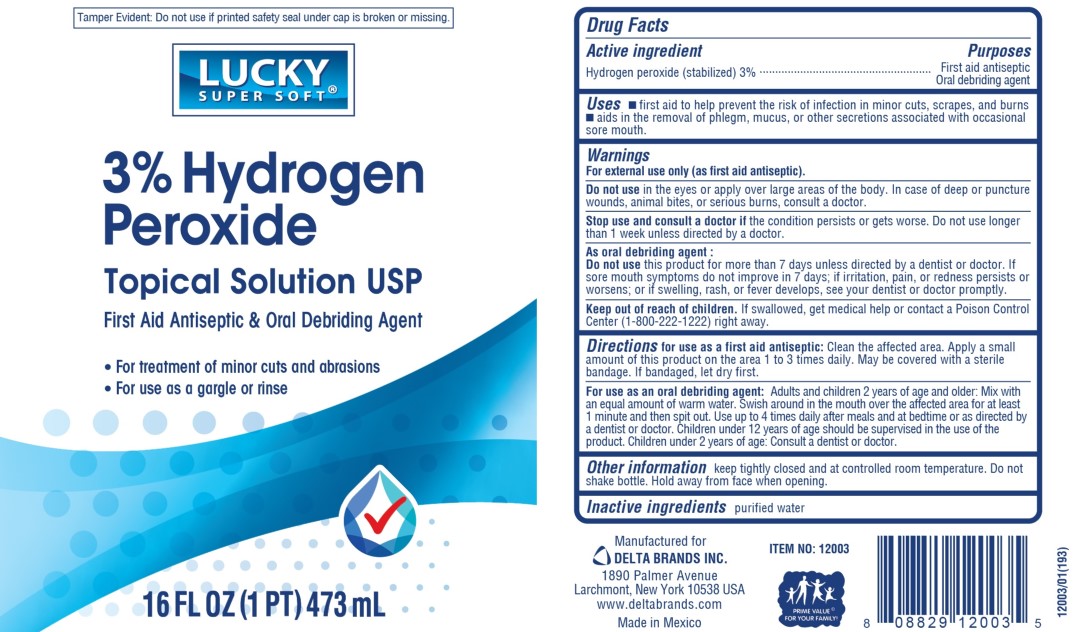 DRUG LABEL: LUCKY SUPER SOFT Hydrogen Peroxide
NDC: 20276-300 | Form: LIQUID
Manufacturer: Delta Brands Inc
Category: otc | Type: HUMAN OTC DRUG LABEL
Date: 20221216

ACTIVE INGREDIENTS: HYDROGEN PEROXIDE 3 mL/100 mL
INACTIVE INGREDIENTS: WATER

HydrgnPerxde3%Dlta

Active ingredient

Hydrogen peroxide (stabilized) 3%

Purpose

First aid antiseptic

Oral debriding agent

Uses

■ first aid to help prevent the risk of infection in minor cuts, scrapes, and burns ■ aids in the removal of phlegm, mucus, or other secretions associated with occasional sore mouth

Warnings

For external use only (as a first aid antiseptic).

Do not use

in the eyes or apply over large areas of the body. In case of deep or puncture wounds, animal bites, or serious burns, consult a doctor

Stop use and consult a doctor if

the condition persists or gets worse. Do not use longer than 1 week unless directed by a doctor.

As oral debriding agent:

Do not use this product for more than 7 days unless directed by a dentist or doctor. If sore mouth symptoms do not improve in 7 days; if irritation, pain or redness persists or worsens; or swelling, rash, or fever develops, see your dentist or doctor promptly

Keep out of reach of children.

If swallowed, get medical help or contact a Poison Control Center (1-800-222-1222) right away.

Directions

for use as a first aid antiseptic: Clean the affected area. Apply a small amount of this product on affected area 1to 3 times a daily.

May be covered with a sterile bandage. If bandaged, let dry first

For use as an oral debriding agent:

Adults and children 2 years of age and older: Mix with an equal amount of warm water. Swish around in the mouth over affected area for at least 1 minute and then spit out. Use up to 4 times daily after meals and at bedtime or as directed by a dentist or doctor

Children under 12 years of age should be supervised in the use of this product. Children under 2 years of age: Consult a dentist or doctor

Other information

keep tightly closed and at controlled room temperature. Do not shake bottle. Hold away from face when opening

Inactive ingredients

purified water